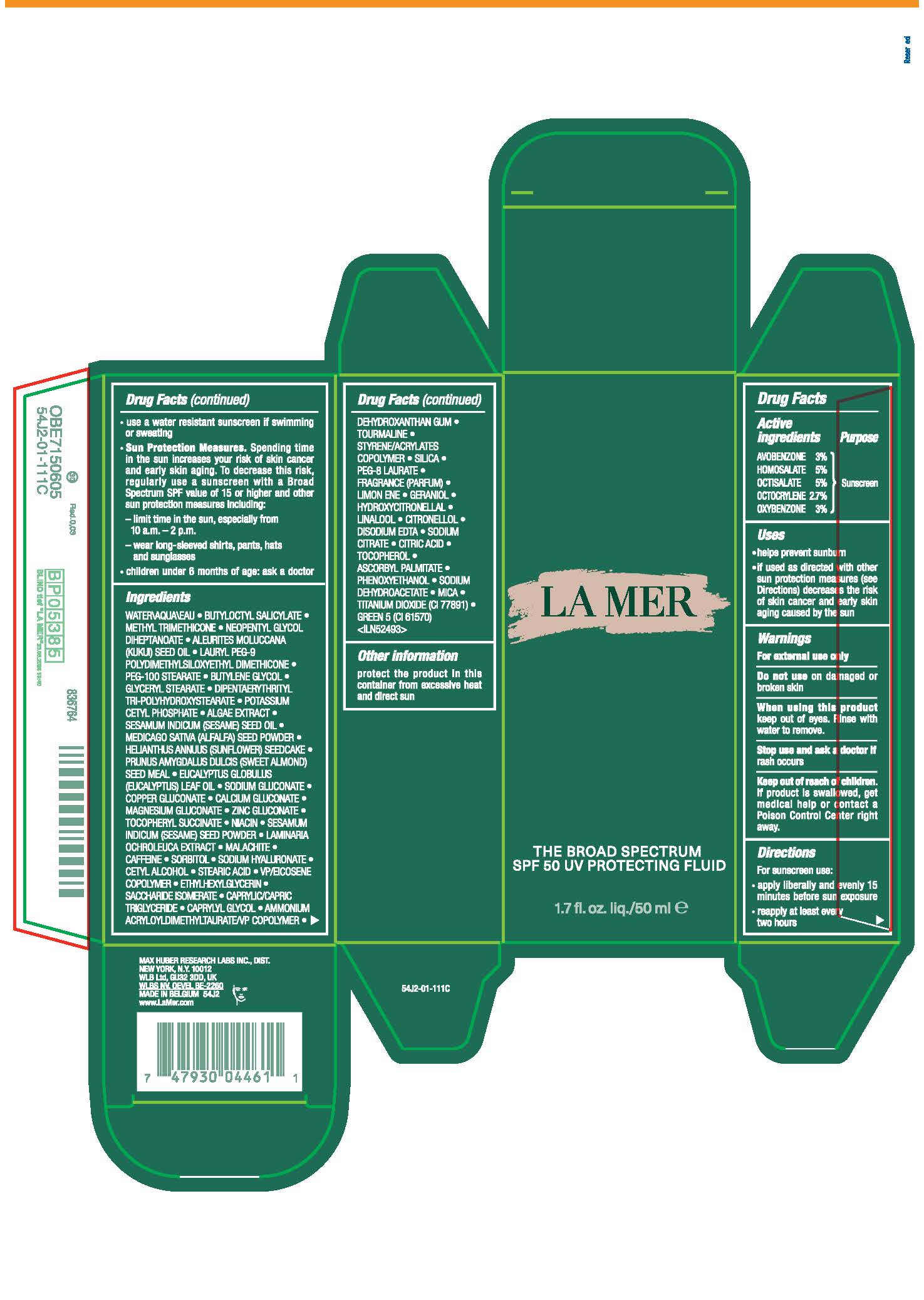 DRUG LABEL: LA MER THE BROAD SPECTRUM SPF 50 UV PROTECTING FLUID
NDC: 65966-016 | Form: LOTION
Manufacturer: MAX HUBER RESEARCH LAB INC
Category: otc | Type: HUMAN OTC DRUG LABEL
Date: 20240829

ACTIVE INGREDIENTS: AVOBENZONE 30 mg/1 mL; HOMOSALATE 50 mg/1 mL; OCTISALATE 50 mg/1 mL; OCTOCRYLENE 27 mg/1 mL; OXYBENZONE 30 mg/1 mL
INACTIVE INGREDIENTS: WATER; BUTYLOCTYL SALICYLATE; METHYL TRIMETHICONE; NEOPENTYL GLYCOL DIHEPTANOATE; KUKUI NUT OIL; LAURYL PEG-9 POLYDIMETHYLSILOXYETHYL DIMETHICONE; PEG-100 STEARATE; BUTYLENE GLYCOL; GLYCERYL MONOSTEARATE; POTASSIUM CETYL PHOSPHATE; SESAME OIL; ALFALFA SEED; HELIANTHUS ANNUUS SEEDCAKE; EUCALYPTUS OIL; SODIUM GLUCONATE; COPPER GLUCONATE; CALCIUM GLUCONATE; MAGNESIUM GLUCONATE; ZINC GLUCONATE; .ALPHA.-TOCOPHEROL SUCCINATE, D-; NIACIN; SESAME SEED; LAMINARIA OCHROLEUCA; CAFFEINE; SORBITOL; HYALURONATE SODIUM; CETYL ALCOHOL; STEARIC ACID; ETHYLHEXYLGLYCERIN; SACCHARIDE ISOMERATE; MEDIUM-CHAIN TRIGLYCERIDES; CAPRYLYL GLYCOL; AMMONIUM ACRYLOYLDIMETHYLTAURATE/VP COPOLYMER; SODIUM DEHYDROACETATE; CITRIC ACID MONOHYDRATE; SILICON DIOXIDE; PEG-8 LAURATE; DIPENTAERYTHRITYL TRI-POLYHYDROXYSTEARATE; PHENOXYETHANOL; GERANIOL; HYDROXYCITRONELLAL; PORPHYRIDIUM PURPUREUM; VINYLPYRROLIDONE/EICOSENE COPOLYMER; DEHYDROXANTHAN GUM; ASCORBYL PALMITATE; LINALOOL, (+/-)-; .BETA.-CITRONELLOL, (R)-; MICA; D&C GREEN NO. 5; TITANIUM DIOXIDE; ALMOND; LIMONENE, (+)-; EDETATE DISODIUM ANHYDROUS; SODIUM CITRATE; BASIC CUPRIC CARBONATE; TOCOPHEROL

LA MER THE BROAD SPECTRUM SPF 50 UV PROTECTING FLUID

Drug Facts

Active ingredients

AVOBENZONE 3.00%
HOMOSALATE 5.00%
OCTISALATE 5.00%
OCTOCRYLENE 2.70%
OXYBENZONE 3.00%

Purpose

Sunscreen

Uses

- helps prevent sunburn
- if used as directed with other sun protection measures (see Directions) decreases the risk of skin cancer and early skin aging caused by the sun

Warnings

For external use only.

Do not use on damaged or broken skin

When using this product keep out of eyes. Rinse with water to remove.

Stop use and ask a doctor if rash occurs.

Keep out of reach of children. If product is swallowed, get medical help or contact a Poison Control Center right away.

Directions

For sunscreen use:

- apply liberally 15 minutes before sun exposure
- reapply every two hours
- use a water resistant sunscreen if swimming or sweating
- Sun Protection Measures. Spending time in the sun increases your risk of skin cancer and early skin aging. To decrease this risk, regularly use a sunscreen with a Broad Spectrum SPF value of 15 or higher and other sun protection measures including:
  - limit time in the sun, especially from 10 a.m. – 2 p.m.
  - wear long-sleeved shirts, pants, hats and sunglasses
- children under 6 months of age: ask a doctor

Ingredients

WATER\AQUA\EAU • BUTYLOCTYL SALICYLATE • METHYL TRIMETHICONE • NEOPENTYL GLYCOL DIHEPTANOATE • ALEURITES MOLUCCANA (KUKUI) SEED OIL • LAURYL PEG-9 POLYDIMETHYLSILOXYETHYL DIMETHICONE • PEG 100 STEARATE • BUTYLENE GLYCOL • GLYCERYL STEARATE • DIPENTAERYTHRITYL TRI-POLYHYDROXYSTEARATE • POTASSIUM CETYL PHOSPHATE • ALGAE (SEAWEED) EXTRACT • SESAMUM INDICUM (SESAME) SEED OIL • MEDICAGO SATIVA (ALFALFA) SEED POWDER • HELIANTHUS ANNUUS (SUNFLOWER) SEEDCAKE • PRUNUS AMYGDALUS DULCIS (SWEET ALMOND) SEED MEAL • EUCALYPTUS GLOBULUS (EUCALYPTUS) LEAF OIL • SODIUM GLUCONATE • COPPER GLUCONATE • CALCIUM GLUCONATE • MAGNESIUM GLUCONATE • ZINC GLUCONATE • TOCOPHERYL SUCCINATE • NIACIN • SESAMUM INDICUM (SESAME) SEED POWDER • LAMINARIA OCHROLEUCA EXTRACT • MALACHITE • CAFFEINE • SORBITOL • SODIUM HYALURONATE • CETYL ALCOHOL • STEARIC ACID • VP/EICOSENE COPOLYMER • ETHYLHEXYLGLYCERIN • SACCHARIDE ISOMERATE • CAPRYLIC/CAPRIC TRIGLYCERIDE • CAPRYLYL GLYCOL • AMMONIUM ACRYLOYLDIMETHYLTAURATE/VP COPOLYMER • DEHYDROXANTHAN GUM • SODIUM DEHYDROACETATE • CITRIC ACID • TOURMALINE • STYRENE/ACRYLATES COPOLYMER • SILICA • PEG-8 LAURATE • FRAGRANCE (PARFUM) • DISODIUM EDTA • PHENOXYETHANOL • LIMONENE • GERANIOL • HYDROXYCITRONELLAL • LINALOOL • CITRONELLOL • MICA • GREEN 5 (CI 61570) • TITANIUM DIOXIDE (CI 77891) <ILN40137>

Other information

Protect the product in this container from excessive heat and direct sun

PRINCIPAL DISPLAY PANEL - 50 ml Bottle Carton

LA MER

the broad spectrum
spf 50 UV protecting fluid

1.7 fl. oz. liq./50 ml e